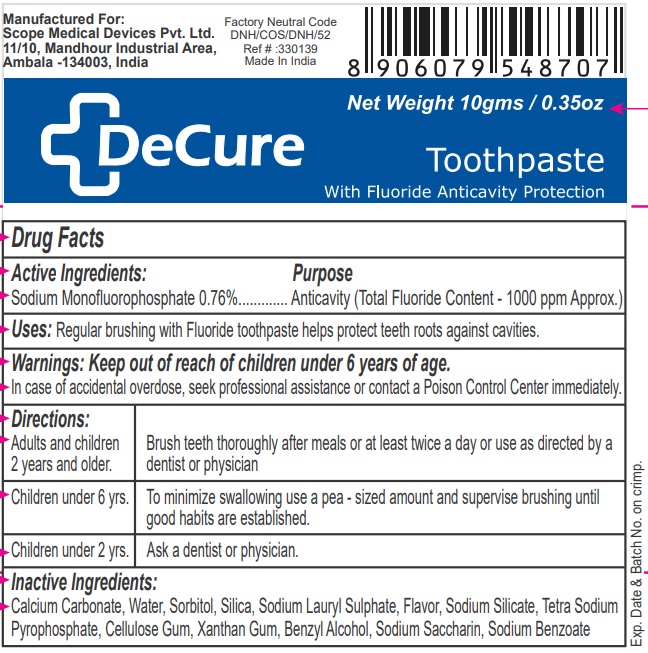 DRUG LABEL: DeCure
NDC: 84132-100 | Form: PASTE, DENTIFRICE
Manufacturer: Scope medical devices private limited
Category: otc | Type: HUMAN OTC DRUG LABEL
Date: 20240507

ACTIVE INGREDIENTS: SODIUM MONOFLUOROPHOSPHATE 7.6 mg/1 g
INACTIVE INGREDIENTS: CALCIUM CARBONATE; WATER; SORBITOL; SILICON DIOXIDE; SODIUM LAURYL SULFATE; SODIUM SILICATE; SODIUM PYROPHOSPHATE; CARBOXYMETHYLCELLULOSE SODIUM, UNSPECIFIED; XANTHAN GUM; BENZYL ALCOHOL; SACCHARIN SODIUM; SODIUM BENZOATE

DeCure Toothpaste

Active Ingredients:

Sodium Monofluorophosphate 0.76%

Purpose

Anticavity (Total Fluoride Content - 1000 ppm Approx.)

Uses:

Regular brushing with Fluoride toothpaste helps protect teeth roots against cavities.

Warnings:

Keep out of reach of children under 6 years of age.
In case of accidental overdose, seek professional assistance or contact a Poison Control Center immediately.

Directions:

Adults and children; 2 years and older. | Brush teeth thoroughly after meals or at least twice a day or use as directed by a dentist or physician
Children under 6 yrs. | To minimize swallowing use a pea - sized amount and supervise brushing until good habits are established.
Children under 2 yrs. | Ask a dentist or physician.

Inactive Ingredients:

Calcium Carbonate, Water, Sorbitol, Silica, Sodium Lauryl Sulphate, Flavor, Sodium Silicate, Tetra Sodium Pyrophosphate, Cellulose Gum, Xanthan Gum, Benzyl Alcohol, Sodium Saccharin, Sodium Benzoate

With Fluoride Anticavity Protection

Manufactured For:
Scope Medical Devices Pvt. Ltd.
11/10, Mandhour Industrial Area,
Ambala -134003, India

Factory Neutral Code
DNH/COS/DNH/52
Ref # :330139
Made in India

Exp. Date & Batch No. on crimp.